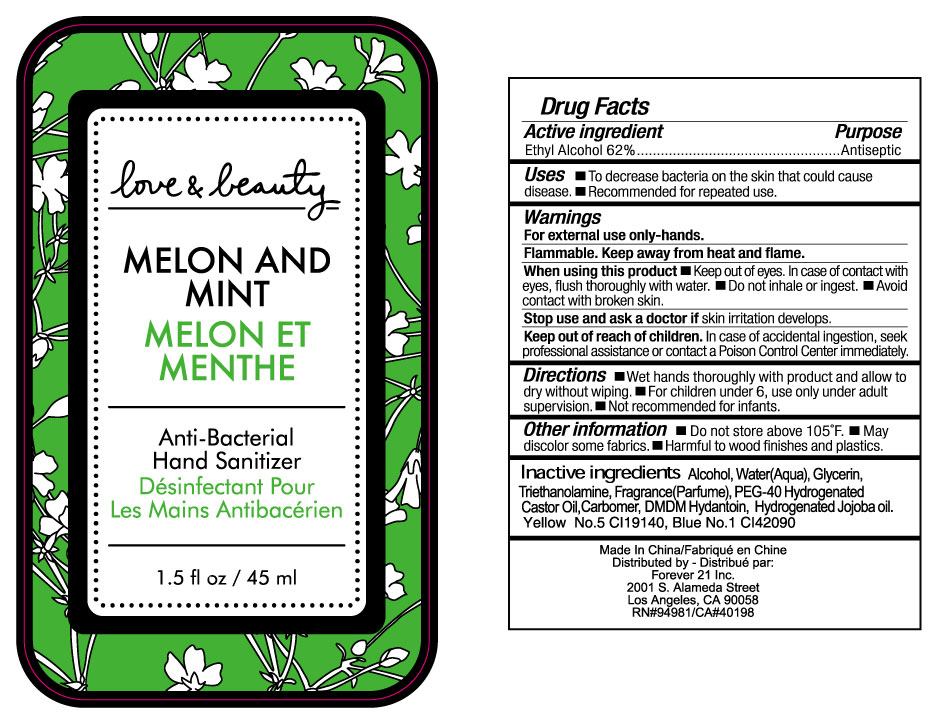 DRUG LABEL: Love and Beauty Melon and Mint Anti-Bacterial Hand Sanitizer
NDC: 49371-038 | Form: LIQUID
Manufacturer: ALILY (ZHANGZHOU) BATH PRODUCTS LTD.
Category: otc | Type: HUMAN OTC DRUG LABEL
Date: 20100505

ACTIVE INGREDIENTS: ALCOHOL 62 g/100 g
INACTIVE INGREDIENTS: WATER 33.9414 g/100 g; GLYCERIN 2 g/100 g; TROLAMINE 0.3 g/100 g; CARBOMER HOMOPOLYMER TYPE A 0.3 g/100 g; POLYOXYL 40 HYDROGENATED CASTOR OIL 0.8 g/100 g; DMDM HYDANTOIN 0.2 g/100 g; FD&C YELLOW NO. 5 0.012 g/100 g; FD&C BLUE NO. 1 0.0016 g/100 g; MELON 0.2 g/100 g; MINT 0.2 g/100 g

Drug Fact

Active Ingredient Purpose

Ethyl Alcohol 62% Antiseptic

Uses:

- To decrease bacteria on the skin that could cause diseases

- Recommended for repeated use.

Warnings:

For external use only-hands.

Flammable-keep away from heat and flame

When using this products

- keep out of eyes. In case of contact with eyes, flush thoroughly with water.
- Avoid contact with broken skin.
- Do not inhale or ingest.

Stop use and ask a doctor if skin irritation develops.
Keep out of reach of children. In case of accidental ingestion, seek professional assistance or contact a Poison Control Center immediately

Directions

- Wet hands thoroughly with product and allow to dry without wiping
- For children under 6, use only under adult supervision
- Not recommended for infants

Other Information

- Do not store above 105 F
- May discolor some fabrics
- Harmful to wood finishes and plastics

Inactive Ingredients

Water (aqua), Glycerin, Triethanolamine, Fragrance (Parfume), PEG-40 Hydrogenated Castor Oil, Carbomer, DMDM Hydantoin, Hydrogenated Jojoba Oil, FD and C Yellow No. 5, FD and C Blue No. 1

PACKAGE LABEL

pict